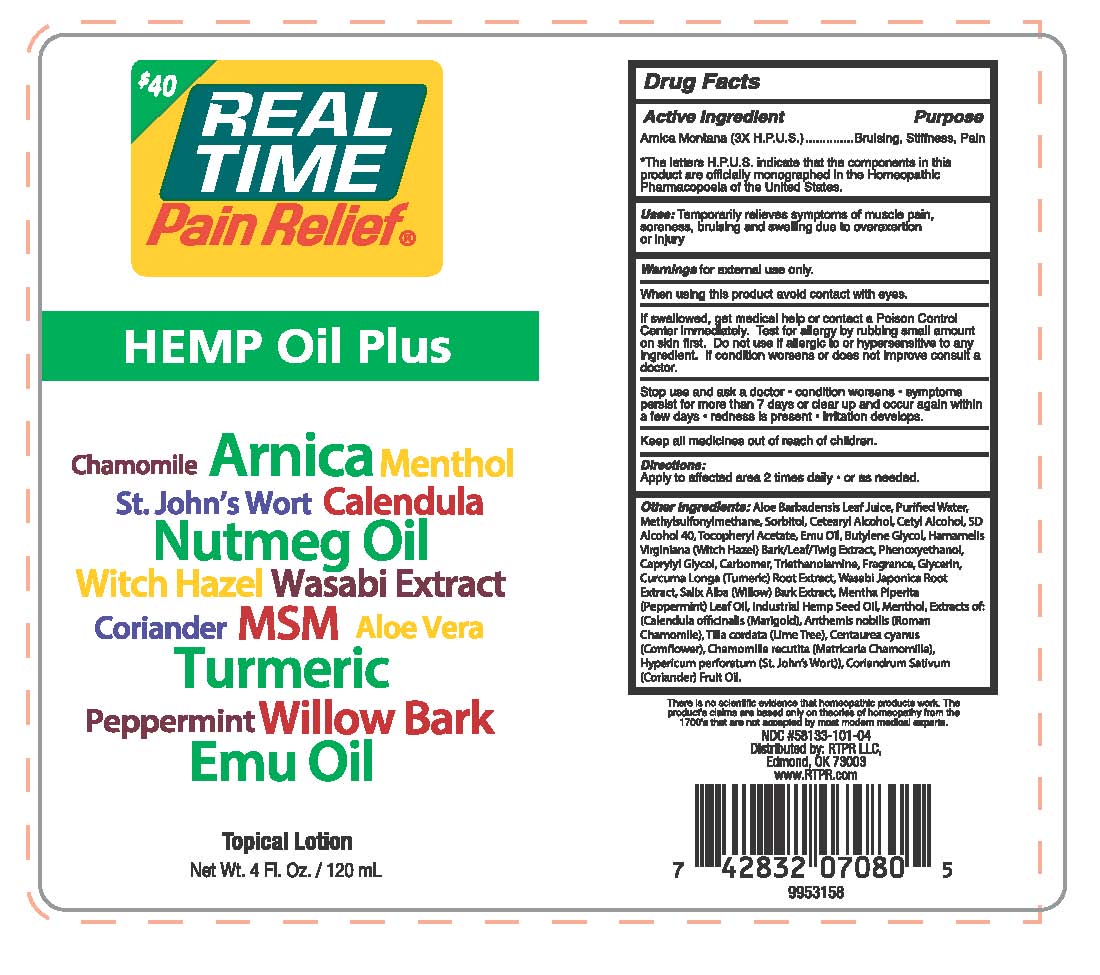 DRUG LABEL: Real Time Pain Relief Hemp Oil Plus
NDC: 58133-101 | Form: CREAM
Manufacturer: Cosmetic Specialty Labs, Inc.
Category: homeopathic | Type: HUMAN OTC DRUG LABEL
Date: 20180115

ACTIVE INGREDIENTS: ARNICA MONTANA 3 [hp_X]/1 g
INACTIVE INGREDIENTS: WATER; ALCOHOL; ALPHA-TOCOPHEROL ACETATE; TRIETHANOLAMINE LAURYLAMINOPROPIONATE; CURCUMA LONGA LEAF; WASABI ROOT; MENTHA PIPERITA LEAF; TILIA CORDATA FLOWER; ALOE VERA LEAF; DIMETHYL SULFONE; SORBITOL; CETOSTEARYL ALCOHOL; CETYL ALCOHOL; EMU OIL; BUTYLENE GLYCOL; HAMAMELIS VIRGINIANA ROOT BARK/STEM BARK; PHENOXYETHANOL; CAPRYLYL GLYCOL; CARBOMER 940; GLYCERIN; SALIX ALBA BARK; MENTHOL; CALENDULA OFFICINALIS SEED OIL; ANTHEMIS ARVENSIS FLOWERING TOP; HEMP; CENTAUREA CYANUS FLOWER; MATRICARIA CHAMOMILLA FLOWERING TOP OIL; HYPERICUM PERFORATUM LEAF; CORIANDRUM SATIVUM WHOLE

Real Time Pain Relief Hemp Oil Plus

Active Ingredient

Arnica Montana (3X H.P.U.S.)

Purpose

Bruising, Stiffness, Pain

*The letters H.P.U.S. indicate that the components in this product are officially monographed in the Homeopathic Pharmacopoeia of the United States.

Uses:

Temporarily relieves symptoms of muscle pain, soreness, bruising and swelling due to overexertion or injury.

Warnings:

for external use only

When using this product:

- Avoid contact with eyes.
- If swallowed, get medical help or contact a Poison Control Center immediately.
- Test for allergy by rubbing small amount on skin first.
- Do not use if allergic to or hypersensitive to any ingredient.
- If condition worsens or does not improve consult a doctor.

Stop use and ask a doctor if:

- condition worsens
- symptoms persist for more than 7 days or clear up and occur again within a few days
- redness is present
- irritation develops

Keep all medicines out of reach of children.

Directions:

Apply to affected area 2 times daily or as needed.

Other ingredients:

Aloe Barbadensis Leaf Juice, Purified Water, Methylsulfonylmethane, Sorbitol, Cetearyl Alcohol, Cetyl Alcohol, SD Alcohol 40, Tocopheryl Acetate, Emu Oil, Butylene Glycol, Hamamelis Virginiana (Witch Hazel) Bark/Leaf/Twig Extract, Phenoxyethanol, Caprylyl Glycol, Carbomer, Triethanolamine, Fragrance, Glycerin, Curcuma Longa (Tumeric) Root Extract, Wasabi Japonica Root Extract, Salix Alba (Willow) Bark Extract, Mentha Piperita (Peppermint) Leaf Oil, Industrial Hemp Seed Oil, Menthol, Extracts of: (Calendula officinalis (Marigold), Anthemis nobilis (Roman Chamomile), Tilia cordata (Lime Tree), Centaurea cyanus (Cornflower), Chamomilla recutita (Matricaria Chamomilla), Hypericum perforatum (St. John’s Wort)), Coriandrum Sativum (Coriander) Fruit Oil.